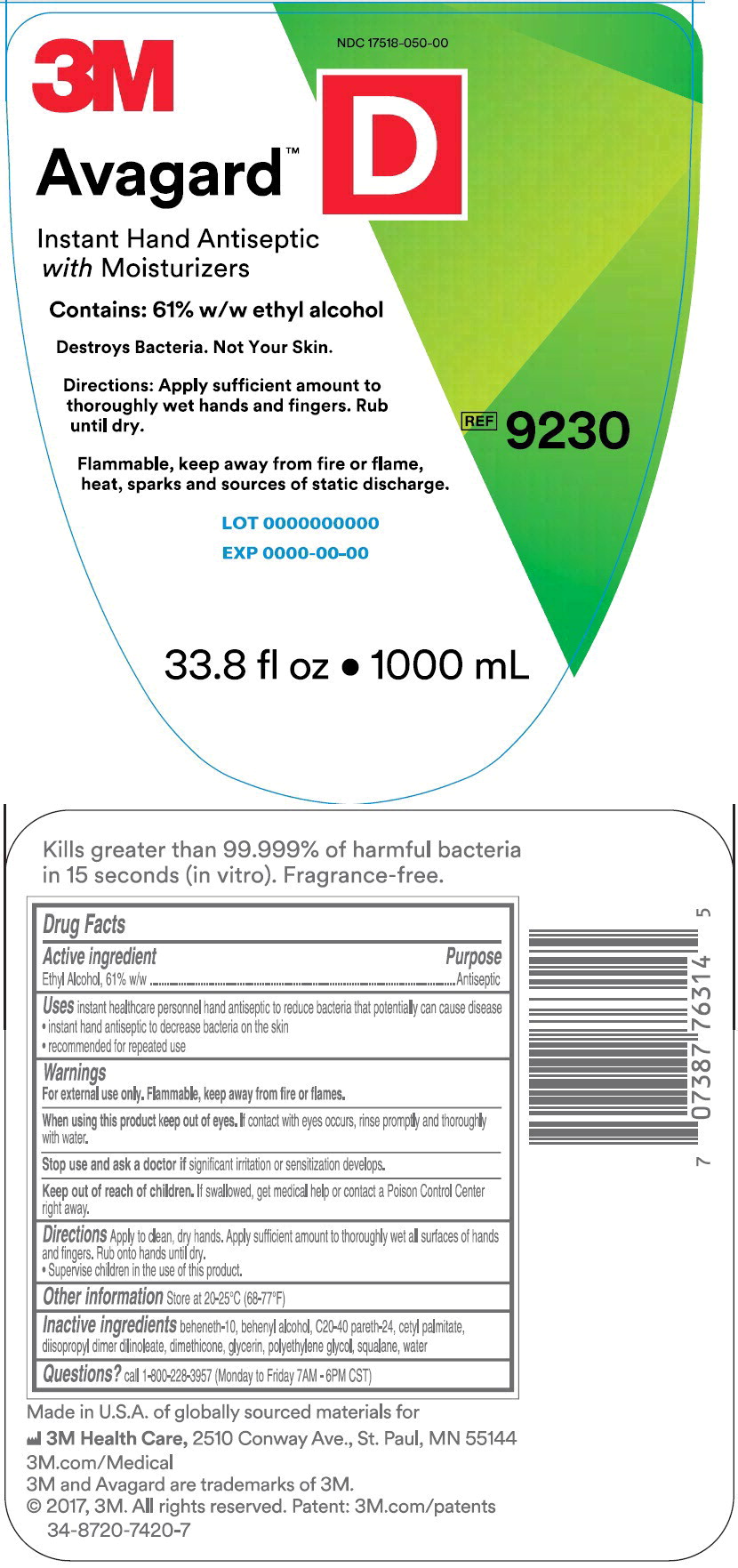 DRUG LABEL: 3M Avagard D
NDC: 17518-050 | Form: LOTION
Manufacturer: Solventum US LLC
Category: otc | Type: HUMAN OTC DRUG LABEL
Date: 20240801

ACTIVE INGREDIENTS: Alcohol 530.7 mg/1 mL
INACTIVE INGREDIENTS: Beheneth-10; docosanol; cetyl palmitate; dimethicone; glycerin; Polyethylene Glycol, Unspecified; squalane; water

Drug Facts

Active ingredient

Ethyl Alcohol, 61% w/w

Purpose

Antiseptic

Uses

- instant healthcare personnel hand antiseptic to reduce bacteria that potentially can cause disease
- instant hand antiseptic to decrease bacteria on the skin
- recommended for repeated use

Warnings

For external use only. Flammable, keep away from fire or flames.

When using this product keep out of eyes. If contact with eyes occurs, rinse promptly and thoroughly with water.

Stop use and ask a doctor if significant irritation or sensitization develops.

Keep out of reach of children. If swallowed, get medical help or contact a Poison Control Center right away.

Directions

Apply to clean, dry hands. Apply sufficient amount to thoroughly wet all surfaces of hand and fingers. Rub on to hands until dry.

- Supervise children in the use of this product.

Other information

- Store at 20-25°C (68-77°F)

Inactive ingredients

beheneth-10, behenyl alcohol, C20-40 pareth-24, cetyl palmitate, diisopropyl dimer dilinoleate, dimethicone, glycerin, polyethylene glycol, squalane, water

Questions?

call 1-800-228-3957 (Monday to Friday 7AM-6PM CST)

Made in U.S.A. of globally sourced materials for

3M Health Care, 2510 Conway Ave., St. Paul, MN 55144

3M.com/Medical

3M and Avagard are trademarks of 3M.

© 2017, 3M. All rights reserved. Patent: 3M.com/patents

34-8720-7420-7

Principle Display Panel – 1000 mL Bottle Label

NDC 17518-050-00

3M

Avagard™ D

Instant Hand Antiseptic with Moisturizer

Contains: 61% w/w ethyl alcohol

Destroys Bacteria. Not Your Skin.

Directions: Apply sufficient amount to thoroughly wet hands and fingers.

Rub until dry.

Flammable, keep away from fire or flame, heat, sparks and sources of static discharge

REF 9230

33.8 fl oz • 1000 mL